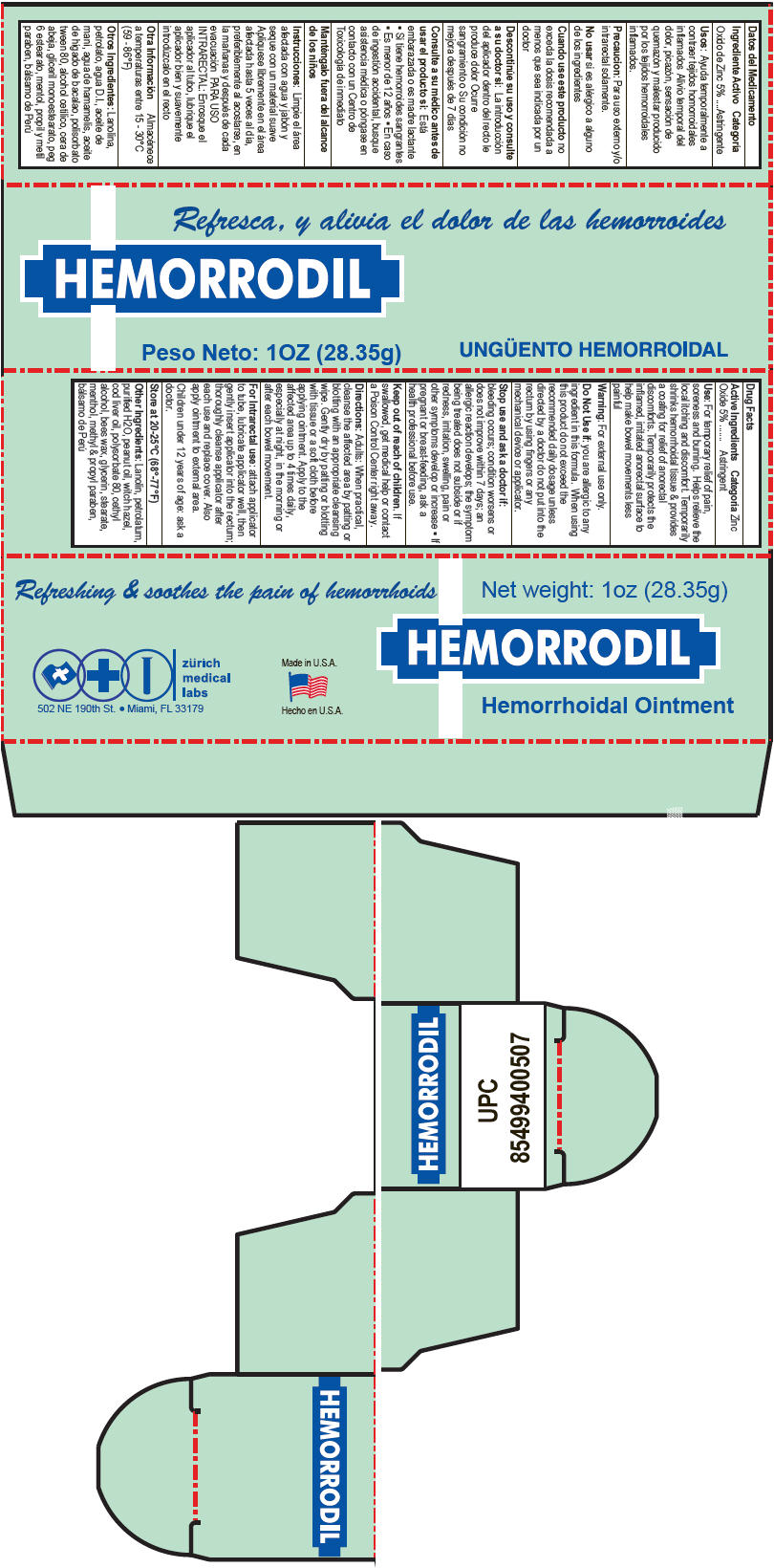 DRUG LABEL: Hemorrodil Unguento
NDC: 61357-130 | Form: OINTMENT
Manufacturer: ZURICH MEDICAL LABS, LLC
Category: otc | Type: HUMAN OTC DRUG LABEL
Date: 20140307

ACTIVE INGREDIENTS: Zinc Oxide 50 mg/1 g
INACTIVE INGREDIENTS: WITCH HAZEL; PEANUT OIL; COD LIVER OIL; MENTHOL; BALSAM PERU; LANOLIN; PETROLATUM; GLYCERYL MONOSTEARATE; PEG-6 STEARATE; YELLOW WAX; CETYL ALCOHOL; POLYSORBATE 80; METHYLPARABEN; PROPYLPARABEN; WATER

Hemorrodil Unguento

Drug Facts

Active Ingredients

Zinc Oxide 5%

Categoría

Astringent

Use

For temporary relief of pain, soreness and burning. Helps relieve the local itching and discomfort. Temporarily shrinks hemorrhoidal tissue & provides a coating for relief of anorectal discomforts. Temporarily protects the inflamed, irritated anorectal surface to help make bowel movements less painful

Warning

For external use only.

Do Not Use if: you are allergic to any ingredient in this formula. When using this product do not exceed the recommended daily dosage unless directed by a doctor do not put into the rectum by using fingers or any mechanical device or applicator.

Stop use and ask a doctor if: bleeding occurs; condition worsens or does not improve within 7 days; an allergic reaction develops; the symptom being treated does not subside or if redness, irritation, swelling, pain or other symptoms develop or increase

PREGNANCY OR BREAST FEEDING

- If pregnant or breast-feeding, ask a health professional before use.

Keep out of reach of children. If swallowed, get medical help or contact a Poison Control Center right away.

Directions

Adults

When practical, cleanse the affected area by patting or blotting with an appropriate cleansing wipe. Gently dry by patting or blotting with tissue or a soft cloth before applying ointment. Apply to the affected area up to 4 times daily, especially at night, in the morning or after each bowel movement.

DOSAGE AND ADMINISTRATION

For Intrarectal use: attach applicator to tube, lubricate applicator well, then gently insert applicator into the rectum; thoroughly cleanse applicator after each use and replace cover. Also apply ointment to external area.

Children under 12 years of age: ask a doctor.

STORAGE AND HANDLING

Store at 20-25°C (68°-77°F)

Other Ingredients

Lanolin, petrolatum, purified H2O, peanut oil, witch hazel, cod liver oil, polysorbate 80, cethyl alcohol, bees wax, glycerin, stearate, menthol, methyl & propyl paraben, bálsamo de Perú

PRINCIPAL DISPLAY PANEL - 28.35 g Tube Carton

Refreshing & soothes the pain of hemorrhoids
Net weight: 1oz (28.35g)

zürich
medical
labs
502 NE 190th St. • Miami, FL 33179

Made in U.S.A.

HEMORRODIL

Hemorrhoidal Ointment